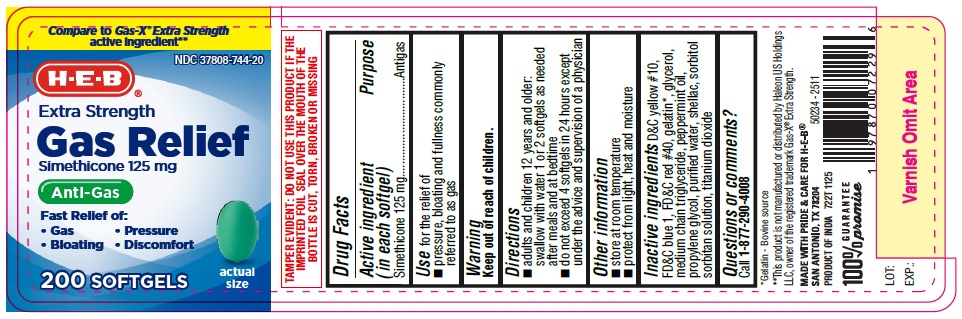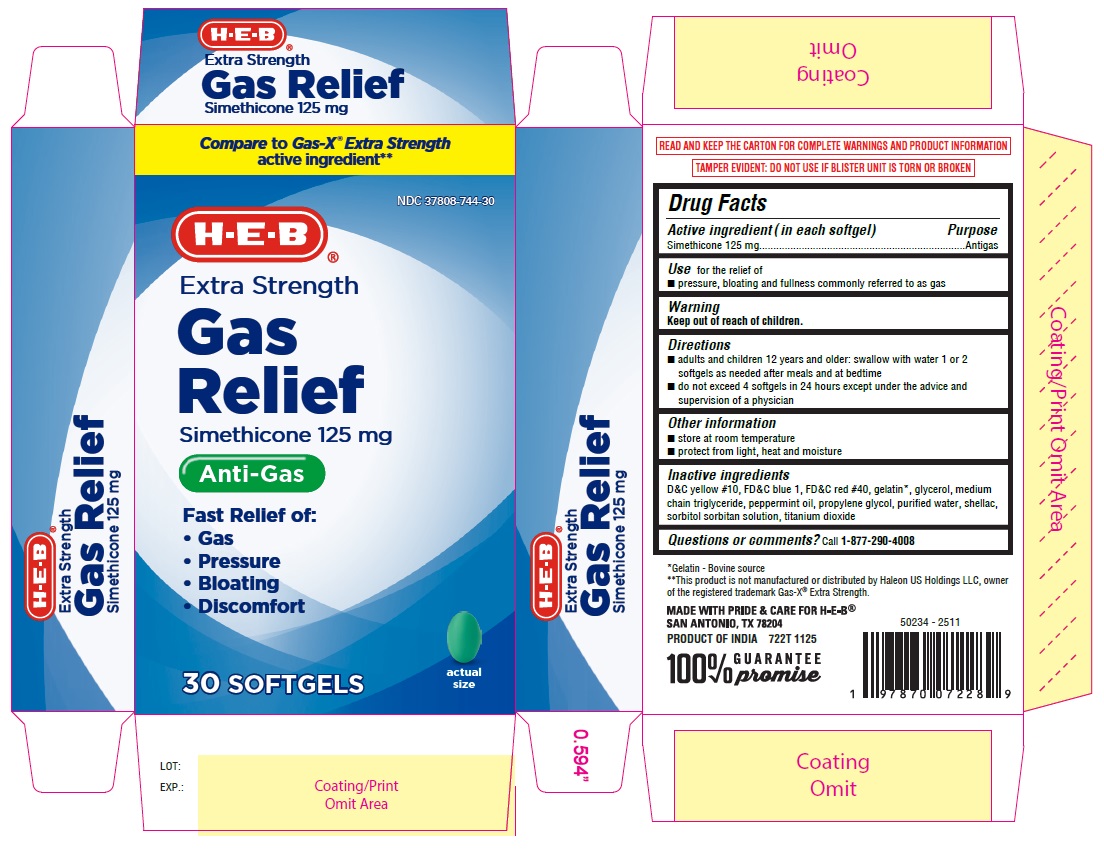 DRUG LABEL: Gas Relief
NDC: 37808-744 | Form: CAPSULE
Manufacturer: H-E-B
Category: otc | Type: HUMAN OTC DRUG LABEL
Date: 20251224

ACTIVE INGREDIENTS: DIMETHICONE 125 mg/1 1
INACTIVE INGREDIENTS: D&C YELLOW NO. 10; WATER; SORBITOL SOLUTION; FD&C BLUE NO. 1; GELATIN, UNSPECIFIED; PEPPERMINT OIL; FD&C RED NO. 40; PROPYLENE GLYCOL; TITANIUM DIOXIDE; GLYCERIN; MEDIUM-CHAIN TRIGLYCERIDES; SHELLAC; SORBITAN

HEB Simethicone 125 mg softgels

Drug Facts

Active ingredient (in each softgel)

Simethicone 125 mg

Purpose

Anti-gas

INDICATIONS AND USAGE

Use for the relief of

- pressure, bloating and fullness commonly referred to as gas

Warning

Keep out of reach of children.

Directions

- adults and children 12 years and older: swallow with water 1 or 2 softgels as needed after meals and at bedtime
- do not exceed 4 softgels in 24 hours except under the advice and supervision of a physician

Other information

- store at room temperature
- protect from light, heat and moisture

Inactive ingredients

D&C Yellow #10, FD&C blue 1, FD&C red #40, gelatin, glycerol, medium chain triglyceride, peppermint oil, propylene glycol, purified water, shellac, sorbitol sorbitan solution, titanium dioxide

Questions or comments? Call 1-877-290-4008

PACKAGE LABEL

722T SImethicone 125mg softgels 30ct

722T Simethicone 125mg softgels 200ct